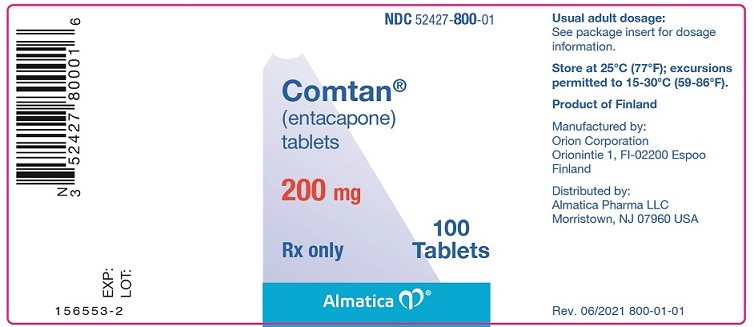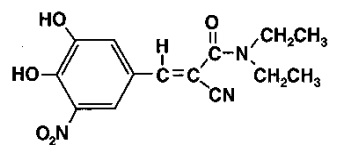 DRUG LABEL: Comtan
NDC: 52427-800 | Form: TABLET, FILM COATED
Manufacturer: Almatica Pharma LLC
Category: prescription | Type: HUMAN PRESCRIPTION DRUG LABEL
Date: 20210730

ACTIVE INGREDIENTS: ENTACAPONE 200 mg/1 1
INACTIVE INGREDIENTS: CROSCARMELLOSE SODIUM; HYDROGENATED COTTONSEED OIL; GLYCERIN; FERRIC OXIDE RED; HYPROMELLOSE, UNSPECIFIED; MAGNESIUM STEARATE; MANNITOL; MICROCRYSTALLINE CELLULOSE; POLYSORBATE 80; SUCROSE; TITANIUM DIOXIDE; FERRIC OXIDE YELLOW

COMTAN®
(entacapone) Tablets

Rx only

Prescribing Information

DESCRIPTION

Comtan® (entacapone) is available as tablets containing 200 mg entacapone.

Entacapone is an inhibitor of catechol-O-methyltransferase (COMT), used in the treatment of Parkinson's disease as an adjunct to levodopa and carbidopa therapy. It is a nitrocatechol-structured compound with a relative molecular mass of 305.29. The chemical name of entacapone is (E)-2-cyano-3-(3,4-dihydroxy-5-nitrophenyl)-N,N-diethyl-2-propenamide. Its empirical formula is C14H15N3O5 and its structural formula is:

The inactive ingredients of the Comtan tablet are microcrystalline cellulose, mannitol, croscarmellose sodium, hydrogenated vegetable oil, hydroxypropyl methylcellulose, polysorbate 80, glycerol 85%, sucrose, magnesium stearate, yellow iron oxide, red iron oxide, and titanium dioxide.

CLINICAL PHARMACOLOGY

Mechanism of Action

Entacapone is a selective and reversible inhibitor of COMT.

In mammals, COMT is distributed throughout various organs with the highest activities in the liver and kidney. COMT also occurs in the heart, lung, smooth and skeletal muscles, intestinal tract, reproductive organs, various glands, adipose tissue, skin, blood cells, and neuronal tissues, especially in glial cells. COMT catalyzes the transfer of the methyl group of S-adenosyl-L-methionine to the phenolic group of substrates that contain a catechol structure. Physiological substrates of COMT include dopa, catecholamines (dopamine, norepinephrine, and epinephrine) and their hydroxylated metabolites. The function of COMT is the elimination of biologically active catechols and some other hydroxylated metabolites. In the presence of a decarboxylase inhibitor, COMT becomes the major metabolizing enzyme for levodopa, catalyzing the metabolism to 3-methoxy-4-hydroxy-L-phenylalanine (3-OMD) in the brain and periphery.

The mechanism of action of entacapone is believed to be through its ability to inhibit COMT and alter the plasma pharmacokinetics of levodopa. When entacapone is given in conjunction with levodopa and an aromatic amino acid decarboxylase inhibitor, such as carbidopa, plasma levels of levodopa are greater and more sustained than after administration of levodopa and an aromatic amino acid decarboxylase inhibitor alone. It is believed that at a given frequency of levodopa administration, these more sustained plasma levels of levodopa result in more constant dopaminergic stimulation in the brain, leading to greater effects on the signs and symptoms of Parkinson's disease. The higher levodopa levels also lead to increased levodopa adverse effects, sometimes requiring a decrease in the dose of levodopa.

In animals, while entacapone enters the central nervous system (CNS) to a minimal extent, it has been shown to inhibit central COMT activity. In humans, entacapone inhibits the COMT enzyme in peripheral tissues. The effects of entacapone on central COMT activity in humans have not been studied.

Pharmacodynamics

COMT Activity in Erythrocytes: Studies in healthy volunteers have shown that entacapone reversibly inhibits human erythrocyte COMT activity after oral administration. There was a linear correlation between entacapone dose and erythrocyte COMT inhibition, the maximum inhibition being 82% following an 800 mg single dose. With a 200 mg single dose of entacapone, maximum inhibition of erythrocyte COMT activity is on average 65% with a return to baseline level within 8 hours.

Effect on the Pharmacokinetics of Levodopa and its Metabolites

When 200 mg entacapone is administered together with levodopa and carbidopa, it increases the area under the curve (AUC) of levodopa by approximately 35%, and the elimination half-life of levodopa is prolonged from 1.3 hours to 2.4 hours. In general, the average peak levodopa plasma concentration and the time of its occurrence (Tmax of 1 hour) are unaffected. The onset of effect occurs after the first administration and is maintained during long-term treatment. Studies in Parkinson's disease patients suggest that the maximal effect occurs with 200 mg entacapone. Plasma levels of 3-OMD are markedly and dose-dependently decreased by entacapone when given with levodopa and carbidopa.

Pharmacokinetics of Entacapone

Entacapone pharmacokinetics are linear over the dose range of 5 mg to 800 mg, and are independent of levodopa and carbidopa coadministration. The elimination of entacapone is biphasic, with an elimination half-life of 0.4 hour to 0.7 hour based on the β-phase and 2.4 hours based on the γ-phase. The γ-phase accounts for approximately 10% of the total AUC. The total body clearance after intravenous administration is 850 mL per min. After a single 200 mg dose of Comtan (entacapone), the Cmax is approximately 1.2 mcg per mL.

Absorption: Entacapone is rapidly absorbed, with a Tmax of approximately 1 hour. The absolute bioavailability following oral administration is 35%. Food does not affect the pharmacokinetics of entacapone.

Distribution: The volume of distribution of entacapone at steady state after intravenous injection is small (20 L). Entacapone does not distribute widely into tissues due to its high plasma protein binding. Based on in vitro studies, the plasma protein binding of entacapone is 98% over the concentration range of 0.4 mcg per mL to 50 mcg per mL. Entacapone binds mainly to serum albumin.

Metabolism and Elimination: Entacapone is almost completely metabolized prior to excretion, with only a very small amount (0.2% of dose) found unchanged in urine. The main metabolic pathway is isomerization to the cis-isomer, followed by direct glucuronidation of the parent and cis-isomer; the glucuronide conjugate is inactive. After oral administration of a ^14C-labeled dose of entacapone, 10% of labeled parent and metabolite is excreted in urine and 90% in feces.

Special Populations: Entacapone pharmacokinetics are independent of age. No formal gender studies have been conducted. Racial representation in clinical studies was largely limited to Caucasians; therefore, no conclusions can be reached about the effect of Comtan on groups other than Caucasian.

Hepatic Impairment: A single 200 mg dose of entacapone, without levodopa and dopa decarboxylase inhibitor coadministration, showed approximately 2-fold higher AUC and Cmax values in patients with a history of alcoholism and hepatic impairment (n = 10) compared to normal subjects (n = 10). All patients had biopsy-proven liver cirrhosis caused by alcohol. According to Child-Pugh grading seven patients with liver disease had mild hepatic impairment and three patients had moderate hepatic impairment. As only about 10% of the entacapone dose is excreted in urine as parent compound and conjugated glucuronide, biliary excretion appears to be the major route of excretion of this drug. Consequently, entacapone should be administered with care to patients with biliary obstruction.

Renal Impairment: The pharmacokinetics of entacapone have been investigated after a single 200 mg entacapone dose, without levodopa and dopa decarboxylase inhibitor coadministration, in a specific renal impairment study. There were three groups: normal subjects (n = 7; creatinine clearance greater than 1.12 mL per sec per 1.73 m^2), moderate impairment (n = 10; creatinine clearance ranging from 0.60 mL per sec per 1.73 m^2 to 0.89 mL per sec per 1.73 m^2), and severe impairment (n = 7; creatinine clearance ranging from 0.20 mL per sec per 1.73 m^2 to 0.44 mL per sec per 1.73 m^2). No important effects of renal function on the pharmacokinetics of entacapone were found.

Drug Interactions: See PRECAUTIONS, Drug Interactions.

Clinical Studies

The effectiveness of Comtan (entacapone) as an adjunct to levodopa in the treatment of Parkinson's disease was established in three 24-week multicenter, randomized, double-blind, placebo-controlled studies in patients with Parkinson's disease. In two of these studies, patients had motor "fluctuations", characterized by documented periods of "On" (periods of relatively good functioning) and "Off" (periods of relatively poor functioning), despite optimum levodopa therapy. There was also a withdrawal period following 6 months of treatment. In the third study, patients were not required to have motor fluctuations. Prior to the controlled part of the studies, patients were stabilized on levodopa for 2 weeks to 4 weeks. Comtan has not been systematically evaluated in patients who have Parkinson's disease without motor fluctuations.

In the first two studies to be described, patients were randomized to receive placebo or entacapone 200 mg administered concomitantly with each dose of levodopa and carbidopa (up to 10 times daily, but averaging 4 doses to 6 doses per day). The formal double-blind portion of both studies was 6 months long. Patients recorded the time spent in the "On" and "Off" states in home diaries periodically throughout the duration of the study. In one study, conducted in the Nordic countries, the primary outcome measure was the total mean time spent in the "On" state during an 18-hour diary recorded day (6 AM to midnight). In the other study, the primary outcome measure was the proportion of awake time spent over 24 hours in the "On" state.

In addition to the primary outcome measure: the amount of time spent in the "Off" state, subparts of the Unified Parkinson's Disease Rating Scale (UPDRS) including mentation (Part I), activities of daily living (ADL) (Part II), motor function (Part III), complications of therapy (Part IV), and disease staging (Part V and VI) were assessed. Additional secondary endpoints included the investigator's and patient's global assessment of clinical condition, a 7-point subjective scale designed to assess global functioning in Parkinson's disease; and the change in daily levodopa and carbidopa dose.

In one of the studies, 171 patients were randomized in 16 centers in Finland, Norway, Sweden, and Denmark (Nordic study), all of whom received concomitant levodopa plus dopa-decarboxylase inhibitor (either levodopa and carbidopa or levodopa and benserazide). In the second study, 205 patients were randomized in 17 centers in North America (US and Canada); all patients received concomitant levodopa and carbidopa.

The following tables display the results of these two studies:

Table 1. Nordic Study
Primary Measure from Home Diary (from an 18-hour Diary Day)
 | Baseline | Change from Baseline at Month 6 [Mean; the month 6 values represent the average of weeks 8, 16, and 24, by protocol-defined outcome measure, except for Investigator's and Patient's Global Improvement.] | p-value vs. placebo
Hours of Awake Time "On"
Placebo | 9.2 | +0.1 | –
Comtan | 9.3 | +1.5 | less than 0.001
Duration of "On" time after first AM dose (hrs)
Placebo | 2.2 | 0.0 | –
Comtan | 2.1 | +0.2 | less than 0.05
Secondary Measures from Home Diary (from an 18-hour Diary Day) [P-values for Secondary Measures and Other Secondary Measures are nominal P values without any adjustment for multiplicity.]
Hours of Awake Time "Off"
Placebo | 5.3 | 0.0 | –
Comtan | 5.5 | -1.3 | less than 0.001
Proportion of Awake Time "On" [Not an endpoint for this study but primary endpoint in the North American Study.] (%)
Placebo | 63.8 | +0.6 | –
Comtan | 62.7 | +9.3 | less than 0.001
Levodopa Total Daily Dose (mg)
Placebo | 705 | +14 | –
Comtan | 701 | -87 | less than 0.001
Frequency of Levodopa Daily Intakes
Placebo | 6.1 | +0.1 | –
Comtan | 6.2 | -0.4 | less than 0.001
Other Secondary Measures†
 | Baseline | Change from Baseline at Month 6 | p-value vs. placebo
Investigator's Global (overall) % Improved [At least one category change at endpoint.]
Placebo | – | 28 | –
Comtan | – | 56 | less than 0.01
Patient's Global (overall) % Improved §
Placebo | – | 22 | –
Comtan | – | 39 | N.S. [Not significant.]
UPDRS Total
Placebo | 37.4 | -1.1 | –
Comtan | 38.5 | -4.8 | less than 0.01
UPDRS Motor
Placebo | 24.6 | -0.7 | –
Comtan | 25.5 | -3.3 | less than 0.05
UPDRS ADL
Placebo | 11.0 | -0.4 | –
Comtan | 11.2 | -1.8 | less than 0.05

Table 2. North American Study
Primary Measure from Home Diary (for a 24-hour Diary Day)
 | Baseline | Change from Baseline at Month 6 [Mean; the month 6 values represent the average of weeks 8, 16, and 24, by protocol-defined outcome measure, except for Investigator's and Patient's Global Improvement.] | p-value vs. placebo
Percent of Awake Time "On"
Placebo | 60.8 | +2.0 | –
Comtan | 60.0 | +6.7 | less than 0.05
Secondary Measures from Home Diary (for a 24-hour Diary Day) [P-values for Secondary Measures and Other Secondary Measures are nominal P values without any adjustment for multiplicity.]
Hours of Awake Time "Off"
Placebo | 6.6 | -0.3 | –
Comtan | 6.8 | -1.2 | less than 0.01
Hours of Awake Time "On"
Placebo | 10.3 | +0.4 | –
Comtan | 10.2 | +1.0 | N.S. [Not significant.]
Levodopa Total Daily Dose (mg)
Placebo | 758 | +19 | –
Comtan | 804 | -93 | less than 0.001
Frequency of Levodopa Daily Intakes
Placebo | 6.0 | +0.2 | –
Comtan | 6.2 | 0.0 | N.S. ‡
Other Secondary Measures†
 | Baseline | Change from Baseline at Month 6* | p-value vs. placebo
Investigator's Global (overall) % Improved [At least one category change at endpoint.]
Placebo | – | 21 | –
Comtan | – | 34 | less than 0.05
Patient's Global (overall) % Improved §
Placebo | – | 20 | –
Comtan | – | 31 | less than 0.05
UPDRS Total [Score change at endpoint similarly to the Nordic Study.]
Placebo | 35.6 | +2.8 | –
Comtan | 35.1 | -0.6 | less than 0.05
UPDRS Motor ¶
Placebo | 22.6 | +1.2 | –
Comtan | 22.0 | -0.9 | less than 0.05
UPDRS ADL ¶
Placebo | 11.7 | +1.1 | –
Comtan | 11.9 | 0.0 | less than 0.05

Effects on "On" time did not differ by age, sex, weight, disease severity at baseline, levodopa dose and concurrent treatment with dopamine agonists or selegiline.

Withdrawal of entacapone

In the North American study, abrupt withdrawal of entacapone, without alteration of the dose of levodopa and carbidopa, resulted in a significant worsening of fluctuations, compared to placebo. In some cases, symptoms were slightly worse than at baseline, but returned to approximately baseline severity within two weeks following levodopa dose increase on average by 80 mg. In the Nordic study, similarly, a significant worsening of parkinsonian symptoms was observed after entacapone withdrawal, as assessed two weeks after drug withdrawal. At this phase, the symptoms were approximately at baseline severity following levodopa dose increase by about 50 mg.

In the third placebo-controlled study, a total of 301 patients were randomized in 32 centers in Germany and Austria. In this study, as in the other two studies, entacapone 200 mg was administered with each dose of levodopa and dopa decarboxylase inhibitor (up to 10 times daily) and UPDRS Parts II and III and total daily "On" time were the primary measures of effectiveness. The following results were observed for the primary measures, as well as for some secondary measures:

Table 3. German-Austrian Study
Primary Measures
 | Baseline | Change from Baseline at Month 6 | p-value vs. placebo (LOCF)
UPDRS ADL [Total population; score change at endpoint.]
Placebo | 12.0 | +0.5 | –
Comtan | 12.4 | -0.4 | less than 0.05
UPDRS Motor *
Placebo | 24.1 | +0.1 | –
Comtan | 24.9 | -2.5 | less than 0.05
Hours of Awake Time "On" (Home diary) [Fluctuating population, with 5 doses to 10 doses; score change at endpoint.]
Placebo | 10.1 | +0.5 | –
Comtan | 10.2 | +1.1 | N.S. [Not significant.]
Secondary Measures [P-values for Secondary Measures are nominal P values without any adjustment for multiplicity.]
 | Baseline | Change from Baseline at Month 6* | p-value vs. placebo
UPDRS Total*
Placebo | 37.7 | +0.6 | –
Comtan | 39.0 | -3.4 | less than 0.05
Percent of Awake Time "On" (Home diary) †
Placebo | 59.8 | +3.5 | –
Comtan | 62.0 | +6.5 | N.S. ‡
Hours of Awake Time "Off" (Home diary) †
Placebo | 6.8 | -0.6 | –
Comtan | 6.3 | -1.2 | 0.07
Levodopa Total Daily Dose (mg) *
Placebo | 572 | +4 | –
Comtan | 566 | -35 | N.S. ‡
Frequency of Levodopa Daily Intake *
Placebo | 5.6 | +0.2 | –
Comtan | 5.4 | 0.0 | less than 0.01
Global (overall) % Improved [Total population; at least one category change at endpoint.]
Placebo | – | 34 | –
Comtan | – | 38 | N.S. ‡

INDICATIONS

Comtan is indicated as an adjunct to levodopa and carbidopa to treat end-of-dose "wearing-off" in patients with Parkinson's disease (see CLINICAL PHARMACOLOGY, Clinical Studies).

Comtan's effectiveness has not been systematically evaluated in patients with Parkinson's disease who do not experience end-of-dose "wearing-off".

CONTRAINDICATIONS

Comtan is contraindicated in patients who have demonstrated hypersensitivity to the drug or its ingredients.

WARNINGS

Monoamine oxidase (MAO) and COMT are the two major enzyme systems involved in the metabolism of catecholamines. It is theoretically possible, therefore, that the combination of Comtan (entacapone) and a non-selective MAO inhibitor (e.g., phenelzine and tranylcypromine) would result in inhibition of the majority of the pathways responsible for normal catecholamine metabolism. For this reason, patients should ordinarily not be treated concomitantly with Comtan and a non-selective MAO inhibitor.

Entacapone can be taken concomitantly with a selective MAO-B inhibitor (e.g., selegiline).

Drugs Metabolized By Catechol-O-Methyltransferase (COMT)

When a single 400 mg dose of entacapone was given with intravenous isoprenaline (isoproterenol) and epinephrine without coadministered levodopa and dopa decarboxylase inhibitor, the overall mean maximal changes in heart rate during infusion were about 50% and 80% higher than with placebo, for isoprenaline and epinephrine, respectively.

Therefore, drugs known to be metabolized by COMT, such as isoproterenol, epinephrine, norepinephrine, dopamine, dobutamine, alpha-methyldopa, apomorphine, isoetherine, and bitolterol should be administered with caution in patients receiving entacapone regardless of the route of administration (including inhalation), as their interaction may result in increased heart rates, possible arrhythmias, and excessive changes in blood pressure.

Ventricular tachycardia was noted in one 32-year-old healthy male volunteer in an interaction study after epinephrine infusion and oral entacapone administration. Treatment with propranolol was required. A causal relationship to entacapone administration appears probable but cannot be attributed with certainty.

Falling Asleep During Activities of Daily Living and Somnolence

Patients with Parkinson's disease treated with Comtan, which increases plasma levodopa levels, or with levodopa have reported suddenly falling asleep without prior warning of sleepiness while engaged in ADL (including the operation of motor vehicles). Some of these episodes resulted in accidents. Although many of these patients reported somnolence while on Comtan, some did not perceive warning signs, such as excessive drowsiness, and believed that they were alert immediately prior to the event. Some of these events have been reported as late as one year after initiation of treatment.

The risk of somnolence was increased (Comtan 2% and placebo 0%) in controlled studies. It has been reported that falling asleep while engaged in ADL always occurs in a setting of preexisting somnolence, although patients may not give such a history. For this reason, prescribers should reassess patients for drowsiness or sleepiness especially since some of the events occur well after the start of treatment. Prescribers should also be aware that patients may not acknowledge drowsiness or sleepiness until directly questioned about drowsiness or sleepiness during specific activities. Patients should be advised to exercise caution while driving, operating machines, or working at heights during treatment with Comtan. Patients who have already experienced somnolence and/or an episode of sudden sleep onset should not participate in these activities during treatment with Comtan.

Before initiating treatment with Comtan, advise patients of the potential to develop drowsiness and specifically ask about factors that may increase this risk such as concomitant use of sedating medications and the presence of sleep disorders. If a patient develops daytime sleepiness or episodes of falling asleep during activities that require active participation (e.g., conversations, eating, etc.), Comtan should ordinarily be discontinued (see DOSAGE AND ADMINISTRATION for guidance on discontinuing Comtan). If the decision is made to continue Comtan, patients should be advised not to drive and to avoid other potentially dangerous activities. There is insufficient information to establish whether dose reduction will eliminate episodes of falling asleep while engaged in ADL.

PRECAUTIONS

Hypotension, Orthostatic Hypotension, and Syncope

Dopaminergic therapy in Parkinson's disease patients has been associated with orthostatic hypotension. Entacapone enhances levodopa bioavailability and, therefore, might be expected to increase the occurrence of orthostatic hypotension. In controlled studies, approximately 1.2% and 0.8% of 200 mg entacapone and placebo patients, respectively, reported at least one episode of syncope. Reports of syncope were generally more frequent in patients in both treatment groups who had an episode of documented hypotension.

Hallucinations and Psychotic-Like Behavior

Dopaminergic therapy in patients with Parkinson's disease has been associated with hallucinations. In clinical studies, hallucinations led to drug discontinuation and premature withdrawal in 0.8% and 0% of patients treated with 200 mg Comtan and placebo, respectively. Hallucinations led to hospitalization in 1.0% and 0.3% of patients in the 200 mg Comtan and placebo groups, respectively. Agitation occurred in 1% of patients treated with Comtan and 0% treated with placebo.

Postmarketing reports indicate that patients may experience new or worsening mental status and behavioral changes, which may be severe, including psychotic-like behavior during Comtan treatment or after starting or increasing the dose of Comtan. Other drugs prescribed to improve the symptoms of Parkinson's disease can have similar effects on thinking and behavior. Abnormal thinking and behavior can cause paranoid ideation, delusions, hallucinations, confusion, disorientation, aggressive behavior, agitation, and delirium. Psychotic-like behaviors were also observed during the clinical development of Comtan.

Patients with a major psychotic disorder should ordinarily not be treated with Comtan because of the risk of exacerbating psychosis. In addition, certain medications used to treat psychosis may exacerbate the symptoms of Parkinson's disease and may decrease the effectiveness of Comtan (see PRECAUTIONS).

Impulse Control and Compulsive Behaviors

Postmarketing reports suggest that patients treated with anti-Parkinson medications can experience intense urges to gamble, increased sexual urges, intense urges to spend money uncontrollably, and other intense urges. Patients may be unable to control these urges while taking one or more of the medications that are used for the treatment of Parkinson's disease and that increase central dopaminergic tone, including Comtan taken with levodopa and carbidopa. In some cases, although not all, these urges were reported to have stopped when the dose of anti-Parkinson medications was reduced or discontinued. Because patients may not recognize these behaviors as abnormal it is important for prescribers to specifically ask patients or their caregivers about the development of new or increased gambling urges, sexual urges, uncontrolled spending or other urges while being treated with entacapone. Physicians should consider dose reduction or stopping Comtan if a patient develops such urges while taking Comtan.

Diarrhea and Colitis

In clinical studies, diarrhea developed in 60 of 603 (10%) and 16 of 400 (4%) of patients treated with 200 mg Comtan and placebo, respectively. In patients treated with Comtan, diarrhea was generally mild to moderate in severity (8.6%) but was regarded as severe in 1.3%. Diarrhea resulted in withdrawal in 10 of 603 (1.7%) patients, 7 (1.2%) with mild and moderate diarrhea and 3 (0.5%) with severe diarrhea. Diarrhea generally resolved after discontinuation of Comtan. Two patients with diarrhea were hospitalized. Typically, diarrhea presents within 4 weeks to 12 weeks after entacapone is started, but it may appear as early as the first week and as late as many months after the initiation of treatment. Diarrhea may be associated with weight loss, dehydration, and hypokalemia.

Postmarketing experience has shown that diarrhea may be a sign of drug-induced microscopic colitis, primarily lymphocytic colitis. In these cases, diarrhea has usually been moderate to severe, watery, and non-bloody, at times associated with dehydration, abdominal pain, weight loss, and hypokalemia. In the majority of cases, diarrhea and other colitis-related symptoms resolved or significantly improved when Comtan treatment was stopped. In some patients with biopsy confirmed colitis, diarrhea had resolved or significantly improved after discontinuation of Comtan but recurred after retreatment with Comtan.

If prolonged diarrhea is suspected to be related to Comtan, the drug should be discontinued and appropriate medical therapy considered. If the cause of prolonged diarrhea remains unclear or continues after stopping entacapone, then further diagnostic investigations including colonoscopy and biopsies should be considered.

Dyskinesia

Comtan may potentiate the dopaminergic side effects of levodopa and may cause or exacerbate preexisting dyskinesia. Although decreasing the dose of levodopa may ameliorate this side effect, many patients in controlled studies continued to experience frequent dyskinesia despite a reduction in their dose of levodopa. The incidence of dyskinesia was 25% for treatment with Comtan and 15% for placebo. The incidence of study withdrawal for dyskinesia was 1.5% for 200 mg Comtan and 0.8% for placebo.

Other Events Reported With Dopaminergic Therapy

The events listed below are events associated with the use of drugs that increase dopaminergic activity:

Rhabdomyolysis: Cases of severe rhabdomyolysis have been reported following the approval of Comtan. Although the reactions typically occurred while patients were treated with Comtan, the complicated nature of these cases makes it difficult to determine what role, if any, Comtan played in their pathogenesis. Severe prolonged motor activity including dyskinesia may account for rhabdomyolysis. Signs and symptoms include fever, alteration of consciousness, myalgia, increased values of creatine phosphokinase (CPK) and myoglobin.

Hyperpyrexia and Confusion: Cases of a symptom complex resembling neuroleptic malignant syndrome (NMS) characterized by elevated temperature, muscular rigidity, altered consciousness, and elevated CPK have been reported in association with the rapid dose reduction or withdrawal of other dopaminergic drugs. In most of these cases, symptoms began after abrupt discontinuation of treatment with entacapone or reduction of its dose, or after the initiation of treatment with entacapone. The complicated nature of these cases makes it difficult to determine what role, if any, Comtan may have played in their pathogenesis. No cases have been reported following the abrupt withdrawal or dose reduction of entacapone treatment during clinical studies.

Prescribers should exercise caution when discontinuing entacapone treatment. When considered necessary, withdrawal should proceed slowly. If the decision is made to discontinue treatment with Comtan, recommendations include monitoring the patient closely and adjusting other dopaminergic treatments as needed. This syndrome should be considered in the differential diagnosis for any patient who develops a high fever or severe rigidity. Tapering Comtan has not been systematically evaluated.

Fibrotic Complications: Cases of retroperitoneal fibrosis, pulmonary infiltrates, pleural effusion, and pleural thickening have been reported in some patients treated with ergot derived dopaminergic agents. These complications may resolve when the drug is discontinued, but complete resolution does not always occur. Although these adverse events are believed to be related to the ergoline structure of these compounds, whether other, nonergot derived drugs (e.g., entacapone) that increase dopaminergic activity can cause them is unknown. It should be noted that the expected incidence of fibrotic complications is so low that even if entacapone caused these complications at rates similar to those attributable to other dopaminergic therapies, it is unlikely that it would have been detected in a cohort of the size exposed to entacapone. Four cases of pulmonary fibrosis were reported during clinical development of entacapone; three of these patients were also treated with pergolide and one with bromocriptine. The duration of treatment with entacapone ranged from 7 months to 17 months.

Melanoma: Epidemiological studies have shown that patients with Parkinson's disease have a higher risk (2- to approximately 6-fold higher) of developing melanoma than the general population. Whether the increased risk observed was due to Parkinson's disease or other factors, such as drugs used to treat Parkinson's disease, is unclear.

For the reasons stated above, patients and providers are advised to monitor for melanomas frequently and on a regular basis when using Comtan for any indication. Ideally, periodic skin examinations should be performed by appropriately qualified individuals (e.g., dermatologists).

Renal Toxicity

In a 1-year toxicity study, entacapone (plasma exposure 20 times that in humans receiving the maximum recommended daily dose of 1,600 mg) caused an increased incidence of nephrotoxicity in male rats that was characterized by regenerative tubules, thickening of basement membranes, infiltration of mononuclear cells, and tubular protein casts. These effects were not associated with changes in clinical chemistry parameters, and there is no established method for monitoring for the possible occurrence of these lesions in humans. Although this toxicity could represent a species-specific effect, there is not yet evidence that this is so.

Hepatic Impairment

Patients with hepatic impairment should be treated with caution. The AUC and Cmax of entacapone approximately doubled in patients with documented liver disease compared to controls (see CLINICAL PHARMACOLOGY, Pharmacokinetics of Entacapone and DOSAGE AND ADMINISTRATION).

Information for Patients

Instruct patients to take Comtan only as prescribed.

Inform patients that hallucinations and/or other psychotic-like behavior can occur.

Advise patients that they may develop postural (orthostatic) hypotension with or without symptoms such as dizziness, nausea, syncope, and sweating. Hypotension may occur more frequently during initial therapy. Accordingly, patients should be cautioned against rising rapidly after sitting or lying down, especially if they have been doing so for prolonged periods, and especially at the initiation of treatment with Comtan.

Advise patients that they should neither drive a car nor operate other complex machinery until they have gained sufficient experience on Comtan to gauge whether or not it affects their mental and/or motor performance adversely. Warn patients about the possibility of sudden onset of sleep during daily activities, in some cases without awareness or warning signs, when they are taking dopaminergic agents, including Comtan. Because of the possible additive sedative effects, caution should be used when patients are taking other CNS depressants in combination with Comtan.

Inform patients that nausea may occur, especially at the initiation of treatment with Comtan.

Inform patients that diarrhea may occur with Comtan and it may have a delayed onset. Sometimes prolonged diarrhea may be caused by colitis (inflammation of the large intestine). Patients with diarrhea should drink fluids to maintain adequate hydration and monitor for weight loss. If diarrhea associated with Comtan is prolonged, discontinuing the drug is expected to lead to resolution, if diarrhea continues after stopping entacapone, further diagnostic investigations may be needed.

Advise patients about the possibility of an increase in dyskinesia.

Tell patients that treatment with entacapone may cause a change in the color of their urine (a brownish orange discoloration) that is not clinically relevant. In controlled studies, 10% of patients treated with Comtan reported urine discoloration compared to 0% of placebo patients.

Although Comtan has not been shown to be teratogenic in animals, it is always given in conjunction with levodopa and carbidopa, which is known to cause visceral and skeletal malformations in rabbits. Accordingly, patients should be advised to notify their physicians if they become pregnant or intend to become pregnant during therapy (see PRECAUTIONS, Pregnancy).

Entacapone is excreted into maternal milk in rats. Because of the possibility that entacapone may be excreted into human maternal milk, advise patients to notify their physicians if they intend to breastfeed or are breastfeeding an infant.

Tell patients and family members to notify their healthcare practitioner if they notice that the patient develops unusual urges or behaviors.

Laboratory Tests

Comtan is a chelator of iron. The impact of entacapone on the body's iron stores is unknown; however, a tendency towards decreasing serum iron concentrations was noted in clinical studies. In a controlled clinical study, serum ferritin levels (as marker of iron deficiency and subclinical anemia) were not changed with entacapone compared to placebo after one year of treatment and there was no difference in rates of anemia or decreased hemoglobin levels.

Special Populations

Patients with hepatic impairment should be treated with caution (see INDICATIONS, DOSAGE AND ADMINISTRATION).

Drug Interactions

In vitro studies of human CYP enzymes showed that entacapone inhibited the CYP enzymes 1A2, 2A6, 2C9, 2C19, 2D6, 2E1 and 3A only at very high concentrations (IC50 from 200 microM to over 1,000 microM; an oral 200 mg dose achieves a highest level of approximately 5 microM in people); these enzymes would therefore not be expected to be inhibited in clinical use.

In an interaction study in healthy volunteers, entacapone did not significantly change the plasma levels of S-warfarin, while the AUC for R-warfarin increased on average by 18% [CI90 11% to 26%], and the international normalized ratio (INR) values increased on average by 13% [CI90 6% to 19%]. Nevertheless, cases of significantly increased INR in patients concomitantly using warfarin have been reported during the postapproval use of Comtan. Therefore, monitoring of INR is recommended when entacapone treatment is initiated or when the dose is increased for patients receiving warfarin.

Protein Binding

Entacapone is highly protein bound (98%). In vitro studies have shown no binding displacement between entacapone and other highly bound drugs, such as warfarin, salicylic acid, phenylbutazone, and diazepam.

Drugs Metabolized by Catechol-O-Methyltransferase (COMT)

See WARNINGS.

Hormone Levels

Levodopa is known to depress prolactin secretion and increase growth hormone levels. Treatment with entacapone coadministered with levodopa and dopa decarboxylase inhibitor does not change these effects.

Effect of Entacapone on the Metabolism of Other Drugs

See WARNINGS regarding concomitant use of Comtan and non-selective MAO inhibitors.

No interaction was noted with the MAO-B inhibitor selegiline in two multiple-dose interaction studies when entacapone was coadministered with a levodopa and dopa decarboxylase inhibitor (n = 29). More than 600 patients with Parkinson's disease in clinical studies have used selegiline in combination with entacapone and levodopa and dopa decarboxylase inhibitor.

As most entacapone excretion is via the bile, caution should be exercised when drugs known to interfere with biliary excretion, glucuronidation, and intestinal beta-glucuronidase are given concurrently with entacapone. These include probenecid, cholestyramine, and some antibiotics (e.g., erythromycin, rifampicin, ampicillin, and chloramphenicol).

No interaction with the tricyclic antidepressant imipramine was shown in a single-dose study with entacapone without coadministered levodopa and dopa-decarboxylase inhibitor.

Carcinogenesis

Two-year carcinogenicity studies of entacapone were conducted in mice and rats. In mice, no increase in tumors was observed at oral doses of 100, 200 and 400 mg/kg/day. At the highest dose tested, plasma exposures (AUC) were 4 times higher than that in humans at the maximum recommended daily dose (MRDD) of 1,600 mg. In rats administered oral doses of 20, 90, or 400 mg/kg/day, an increased incidence of renal tubular adenomas and carcinomas was observed in males at the highest dose tested. Plasma AUCs at the higher dose not associated with increased renal tumors (90 mg/kg/day) were approximately 5 times that in humans at the MRDD of entacapone.

The carcinogenic potential of entacapone administered in combination with levodopa and carbidopa has not been evaluated.

Mutagenesis

Entacapone was mutagenic and clastogenic in the in vitro mouse lymphoma tk assay in the presence and absence of metabolic activation, and was clastogenic in cultured human lymphocytes in the presence of metabolic activation. Entacapone, either alone or in combination with levodopa and carbidopa, was not clastogenic in the in vivo mouse micronucleus test or mutagenic in the bacterial reverse mutation assay (Ames test).

Impairment of Fertility

Entacapone did not impair fertility or general reproductive performance in rats treated with up to 700 mg/kg/day (plasma AUCs 28 times those in humans receiving the MRDD of 1,600 mg). Delayed mating, but no fertility impairment, was evident in female rats treated with 700 mg/kg/day of entacapone.

Pregnancy

In embryo-fetal development studies, entacapone was administered to pregnant animals throughout organogenesis at doses of up to 1,000 mg/kg/day in rats and 300 mg/kg/day in rabbits. Increased incidences of fetal variations were evident in litters from rats treated with the highest dose, in the absence of overt signs of maternal toxicity. The maternal plasma drug exposure (AUC) associated with this dose was approximately 34 times the estimated plasma exposure in humans receiving the maximum recommended daily dose (MRDD) of 1,600 mg. Increased frequencies of abortions, late and total resorptions, and decreased fetal weights were observed in the litters of rabbits treated with maternally toxic doses of 100 mg/kg/day (plasma AUCs 0.4 times those in humans receiving the MRDD) or greater. There was no evidence of teratogenicity in these studies.

However, when entacapone was administered to female rats prior to mating and during early gestation, an increased incidence of fetal eye anomalies (macrophthalmia, microphthalmia, anophthalmia) was observed in the litters of dams treated with doses of 160 mg/kg/day (plasma AUCs 7 times those in humans receiving the MRDD) or greater, in the absence of maternal toxicity. Administration of up to 700 mg/kg/day (plasma AUCs 28 times those in humans receiving the MRDD) to female rats during the latter part of gestation and throughout lactation produced no evidence of developmental impairment in the offspring.

Entacapone is always given concomitantly with levodopa and carbidopa, which is known to cause visceral and skeletal malformations in rabbits. The teratogenic potential of entacapone in combination with levodopa and carbidopa was not assessed in animals.

There is no experience from clinical studies regarding the use of Comtan in pregnant women. Therefore, Comtan should be used during pregnancy only if the potential benefit justifies the potential risk to the fetus.

Nursing Women

In animal studies, entacapone was excreted into maternal rat milk.

It is not known whether entacapone is excreted in human milk. Because many drugs are excreted in human milk, caution should be exercised when entacapone is administered to a nursing woman.

Pediatric Use

Safety and effectiveness in pediatric patients have not been established.

ADVERSE REACTIONS

Because clinical studies are conducted under widely varying conditions, the incidence of adverse reactions (number of unique patients experiencing an adverse reaction associated with treatment per total number of patients treated) observed in the clinical studies of a drug cannot be directly compared to the incidence of adverse reactions in the clinical studies of another drug and may not reflect the incidence of adverse reactions observed in practice.

A total of 1,450 patients with Parkinson's disease were treated with Comtan in premarketing clinical studies. Included were patients with fluctuating symptoms, as well as those with stable responses to levodopa therapy. All patients received concomitant treatment with levodopa preparations, however, and were similar in other clinical aspects.

The most commonly observed adverse reactions (incidence at least 3% greater than placebo) in double-blind, placebo-controlled studies (N = 1,003) associated with the use of Comtan were: dyskinesia, urine discoloration, diarrhea, nausea, hyperkinesia, abdominal pain, vomiting, and dry mouth. Approximately 14% of the 603 patients given entacapone in the double-blind, placebo-controlled studies discontinued treatment due to adverse reactions, compared to 9% of the 400 patients who received placebo. The most frequent causes of discontinuation in decreasing order were: psychiatric disorders (2% vs. 1%), diarrhea (2% vs. 0%), dyskinesia and hyperkinesia (2% vs. 1%), nausea (2% vs. 1%), and abdominal pain (1% vs. 0%).

Adverse Event Incidence in Controlled Clinical Studies

Table 4 lists treatment-emergent adverse events that occurred in at least 1% of patients treated with entacapone participating in the double-blind, placebo-controlled studies and that were numerically more common in the Comtan group, compared to placebo. In these studies, either Comtan or placebo was added to levodopa and carbidopa (or levodopa and benserazide).

Table 4: Summary of Patients with Adverse Events after Start of Trial Drug Administration at least 1% in Comtan Group and Greater Than Placebo
SYSTEM ORGAN CLASS | Comtan | Placebo
Preferred term | (n = 603) % of patients | (n = 400) % of patients
SKIN AND APPENDAGES DISORDERS
Sweating increased | 2 | 1
MUSCULOSKELETAL SYSTEM DISORDERS
Back pain | 2 | 1
CENTRAL AND PERIPHERAL NERVOUS SYSTEM DISORDERS
Dyskinesia | 25 | 15
Hyperkinesia | 10 | 5
Hypokinesia | 9 | 8
Dizziness | 8 | 6
SPECIAL SENSES, OTHER DISORDERS
Taste perversion | 1 | 0
PSYCHIATRIC DISORDERS
Anxiety | 2 | 1
Somnolence | 2 | 0
Agitation | 1 | 0
GASTROINTESTINAL SYSTEM DISORDERS
Nausea | 14 | 8
Diarrhea | 10 | 4
Abdominal pain | 8 | 4
Constipation | 6 | 4
Vomiting | 4 | 1
Mouth dry | 3 | 0
Dyspepsia | 2 | 1
Flatulence | 2 | 0
Gastritis | 1 | 0
Gastrointestinal disorders | 1 | 0
RESPIRATORY SYSTEM DISORDERS
Dyspnea | 3 | 1
PLATELET, BLEEDING AND CLOTTING DISORDERS
Purpura | 2 | 1
URINARY SYSTEM DISORDERS
Urine discoloration | 10 | 0
BODY AS A WHOLE - GENERAL DISORDERS
Back pain | 4 | 2
Fatigue | 6 | 4
Asthenia | 2 | 1
RESISTANCE MECHANISM DISORDERS
Infection bacterial | 1 | 0

Effects of Gender and Age on Adverse Reactions

No differences were noted in the rate of adverse events attributable to entacapone by age or gender.

Postmarketing Reports

The following spontaneous reports of adverse events temporally associated with Comtan have been identified since market introduction and are not listed in Table 4. Because these reactions are reported voluntarily from a population of unknown size, it is not always possible to reliably estimate their frequency or establish causal relationship to Comtan exposure.

Hepatitis with mainly cholestatic features has been reported.

To report SUSPECTED ADVERSE REACTIONS, contact Almatica Pharma LLC at 1-877-447-7979 or FDA at 1-800-FDA-1088 or www.fda.gov/medwatch.

DRUG ABUSE AND DEPENDENCE

Comtan is not a controlled substance. Animal studies to evaluate the drug abuse and potential dependence have not been conducted. Although clinical studies have not revealed any evidence of the potential for abuse, tolerance or physical dependence, systematic studies in humans designed to evaluate these effects have not been performed.

OVERDOSAGE

The postmarketing data include several cases of overdose. The highest reported dose of entacapone was at least 40,000 mg. The acute symptoms and signs commonly seen in these cases included somnolence and decreased activity, states related to depressed level of consciousness (e.g., coma, confusion and disorientation) and discolorations of skin, tongue, and urine, as well as restlessness, agitation, and aggression.

COMT inhibition by entacapone treatment is dose-dependent. A massive overdose of Comtan (entacapone) may theoretically produce a 100% inhibition of the COMT enzyme in humans, thereby preventing the metabolism of endogenous and exogenous catechols.

The highest daily dose given to humans was 2,400 mg, administered in one study as 400 mg six times daily with levodopa and carbidopa for 14 days in 15 Parkinson's disease patients, and in another study as 800 mg three times daily for 7 days in 8 healthy volunteers. At this daily dose, the peak plasma concentrations of entacapone averaged 2.0 mcg per mL (at 45 minutes, compared to 1.0 mcg per mL and 1.2 mcg per mL with 200 mg entacapone at 45 minutes). Abdominal pain and loose stools were the most commonly observed adverse events during this study. Daily doses as high as 2,000 mg Comtan have been administered as 200 mg 10 times daily with levodopa and carbidopa or levodopa and benserazide for at least 1 year in 10 patients, for at least 2 years in 8 patients, and for at least 3 years in 7 patients. Overall, however, clinical experience with daily doses above 1,600 mg is limited.

The range of lethal plasma concentrations of entacapone based on animal data was 80 mcg per mL to 130 mcg per mL in mice. Respiratory difficulties, ataxia, hypoactivity, and convulsions were observed in mice after high oral (gavage) doses.

Management of Overdose

Management of Comtan overdose is symptomatic; there is no known antidote to Comtan. Hospitalization is advised, and general supportive care is indicated. There is no experience with hemodialysis or hemoperfusion, but these procedures are unlikely to be of benefit, because Comtan is highly bound to plasma proteins. An immediate gastric lavage and repeated doses of charcoal over time may hasten the elimination of Comtan by decreasing its absorption and reabsorption from the gastrointestinal (GI) tract. The adequacy of the respiratory and circulatory systems should be carefully monitored and appropriate supportive measures employed. The possibility of drug interactions, especially with catechol-structured drugs, should be borne in mind.

DOSAGE AND ADMINISTRATION

The recommended dose of Comtan (entacapone) is one 200 mg tablet administered concomitantly with each levodopa and carbidopa dose to a maximum of 8 times daily (200 mg × 8 = 1,600 mg per day). Clinical experience with daily doses above 1,600 mg is limited.

Comtan should always be administered in association with levodopa and carbidopa. Entacapone has no antiparkinsonian effect of its own.

In clinical studies, the majority of patients required a decrease in daily levodopa dose if their daily dose of levodopa had been greater than or equal to 800 mg or if patients had moderate or severe dyskinesia before beginning treatment.

To optimize an individual patient's response, reductions in daily levodopa dose or extending the interval between doses may be necessary. In clinical studies, the average reduction in daily levodopa dose was about 25% in those patients requiring a levodopa dose reduction (more than 58% of patients with levodopa doses above 800 mg daily required such a reduction).

Comtan can be combined with both the immediate and sustained-release formulations of levodopa and carbidopa.

Comtan may be taken with or without food (see CLINICAL PHARMACOLOGY).

Patients With Impaired Hepatic Function: Patients with hepatic impairment should be treated with caution. The AUC and Cmax of entacapone approximately doubled in patients with documented liver disease, compared to controls. However, these studies were conducted with single-dose entacapone without levodopa and dopa decarboxylase inhibitor coadministration, and therefore the effects of liver disease on the kinetics of chronically administered entacapone have not been evaluated (see CLINICAL PHARMACOLOGY, Pharmacokinetics of Entacapone).

Withdrawing Patients from Comtan: Rapid withdrawal or abrupt reduction in the Comtan dose could lead to emergence of signs and symptoms of Parkinson's disease (see CLINICAL PHARMACOLOGY, Clinical Studies), and may lead to hyperpyrexia and confusion, a symptom complex resembling NMS (see PRECAUTIONS, Other Events Reported With Dopaminergic Therapy). This syndrome should be considered in the differential diagnosis for any patient who develops a high fever or severe rigidity. If a decision is made to discontinue treatment with Comtan, patients should be monitored closely and other dopaminergic treatments should be adjusted as needed. Although tapering Comtan has not been systematically evaluated, it seems prudent to withdraw patients slowly if the decision to discontinue treatment is made.

HOW SUPPLIED

Comtan (entacapone) is supplied as 200 mg film-coated tablets for oral administration. The oval-shaped tablets are brownish-orange, unscored, and embossed "Comtan" on one side. Tablets are provided in HDPE containers as follows:

Bottles of 100 | NDC 52427-800-01

STORAGE AND HANDLING

Store at 25°C (77°F); excursions permitted to 15°C to 30°C (59°F to 86°F). [See USP Controlled Room Temperature.]

Comtan (entacapone) tablets are manufactured by Orion Corporation, Orionintie 1, FI-02200 Espoo, Finland and distributed by Almatica Pharma LLC, Morristown, NJ 07960 USA

Rev. 05/2020

PI800-00

PACKAGE LABEL PRINCIPAL DISPLAY PANEL

NDC 52427-800-01

Comtan®
(entacapone)
tablets

200 mg

100 Tablets

Rx only